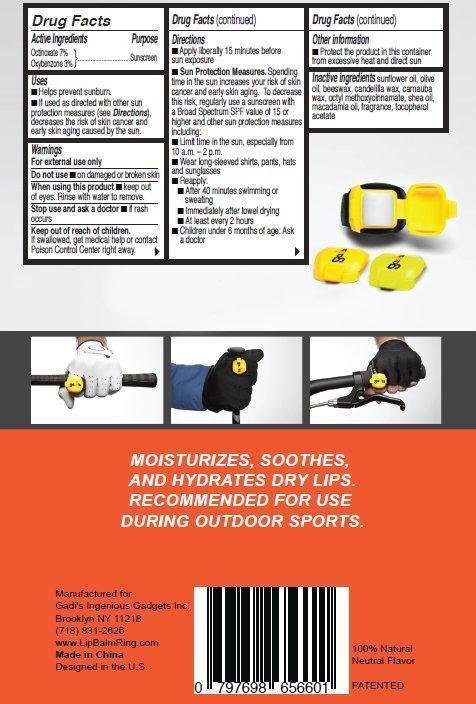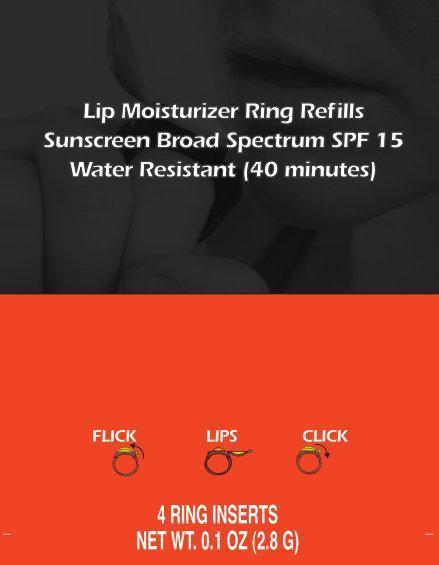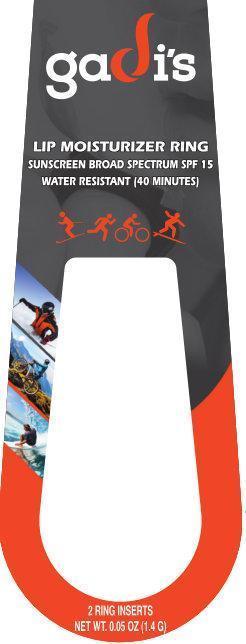 DRUG LABEL: Gadis Lip Moisturizer
NDC: 69065-001 | Form: LIPSTICK
Manufacturer: Gadis Ingenious Gadgets Inc.
Category: otc | Type: HUMAN OTC DRUG LABEL
Date: 20140909

ACTIVE INGREDIENTS: Octinoxate 7 g/100 g; Oxybenzone 3 g/100 g
INACTIVE INGREDIENTS: SUNFLOWER OIL; OLIVE OIL; YELLOW WAX; CANDELILLA WAX; 2-BUTYLOCTYL METHACRYLATE; SHEANUT OIL; MACADAMIA OIL; CARNAUBA WAX

Gadis Lip Moisturizer SPF 15

Drug Facts

Active ingredients

Octinoxate 7%
Oxybenzone 3%

Purpose

Sunscreen

Use

- Helps prevent sunburn
- If used as directed with other sun protection measures (see Directions), decreases the risk of skin cancer and early skin aging caused by the sun.

Warnings

Skin Cancer/Skin Aging Alert

Spending time in the sun increases your risk of skin cancer and early skin aging. This product has been shown only to help prevent sunburn, not skin cancer or early skin aging.

For external use only

Do not use on damaged or broken skin

When using this product

keep out of eyes. Rinse with water to remove

Stop use and ask a doctor if rash occurs

Keep out of reach of children. If swallowed, get medical help or contact a Poison Control Center right away.

Directions

- apply liberally and evenly 15 minutes before sun exposure.
- Sun Protection Measures.
  Spending
  time in the sun increases your risk of skin
  cancer and early skin aging. To decrease
  this risk, regularly use a sunscreen with
  a Broad Spectrum SPF value of 15 or
  higher and other sun protection measures
  including:
- Limit time in the sun, especially from
  10 a.m. – 2 p.m.
- Wear long-sleeved shirts, pants, hats
  and sunglasses
- Reapply:
- After 40 minutes swimming or
  sweating
- Immediately after towel drying
- At least every 2 hours
- Children under 6 months of age: Ask
  a doctor

Other information

- Protect the product in this container from excessive heat and direct sun

Inactive Ingredients

sunflower oil, olive

oil, beeswax, candelilla wax, carnauba

wax, octyl methoxycinnamate, shea oil,

macadamia oil, fragrance, tocopherol

acetate

Manufactured for

Gadi's Ingenious Gadgets Inc.

Brooklyn NY 11218

(718) 831-2626

www.LipBalmRing.com

Made in China

Designed in the U.S.

Gadis Lip Moisturizer SPF 15

gadi's

Lip Moisturizer Ring

Sunscreen Broad Spectrum SPF 15

Water Resistant (40 minutes)

MOISTURIZES, SOOTHES,

AND HYDRATES DRY LIPS.

RECOMMENDED FOR USE

DURING OUTDOOR SPORTS.

4 RING INSERTS

NET WT. 0.1 OZ (2.8 G)